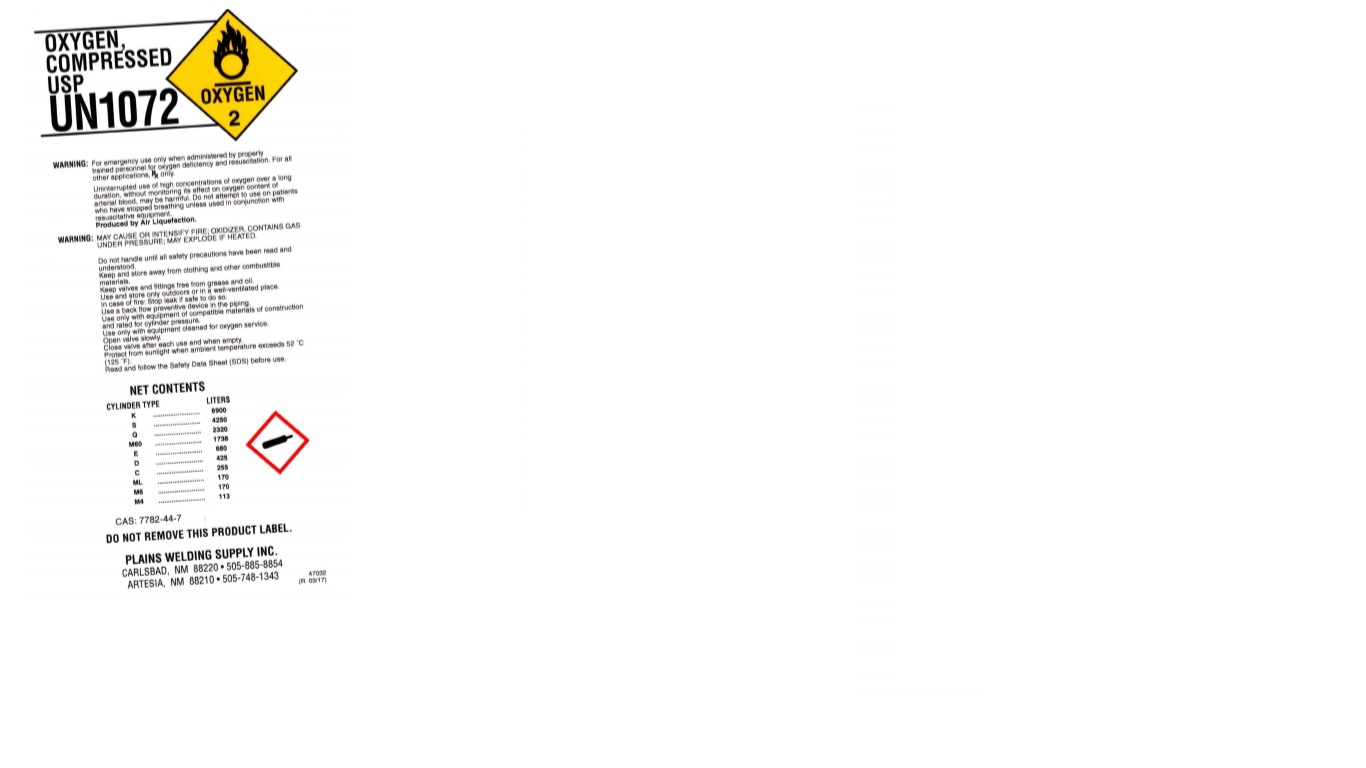 DRUG LABEL: Oxygen
NDC: 59924-001 | Form: GAS
Manufacturer: Plains Welding Supply, Inc.
Category: prescription | Type: HUMAN PRESCRIPTION DRUG LABEL
Date: 20251228

ACTIVE INGREDIENTS: OXYGEN 992 mL/1 L

oxygen

PACKAGE LABEL

OXYGEN, COMPRESSED USP
UN1072
WARNING: For emergency use only when administered by properly trained personnel for oxygen deficiency and resuscitation. For all other applications, Rx only.
Uninterrupted use of high concentrations of oxygen over a long duration, without monitoring its effect on oxygen content of arterial blood, may be harmful. Do not attempt to use on patients who have stopped breathing unless used in conjunction with resuscitative equipment.
Produced by Air Liquefaction.
WARNING: MAY CAUSE OR INTENSIFY FIRE; OXIDIZER. CONTAINS GAS UNDER PRESSURE; MAY EXPLODE IF HEATED.
Do not handle until all safety precautions have been read and understood.
Keep and store away from clothing and other combustible materials.
Keep valves and fittings free from grease and oil.
Use a back flow preventive device in the piping.
Use only with equipment of compatible materials of construction and rated for cylinder pressure.
Use only with equipment cleaned for oxygen service.
Open valve slowly.
Close valve after each use and when empty.
Protect from sunlight when ambient temperature exceeds 52 C(125 F).
Read and follow the Safety Data Sheet (SDS) before use.
NET CONTENTS
CYLINDER TYPE LITERS
K 6900
S 4250
Q 2320
M60 1738
E 680
D 425
C 255
ML 170
M6 170
M4 113
CAS: 7782-44-7
DO NOT REMOVE THIS PRODUCT LABEL.
PLAINS WELDING SUPPLY INC.
CARLSBAD, NM 88220 505-885-8854
ARTESIA, NM 88210 505-748-1343